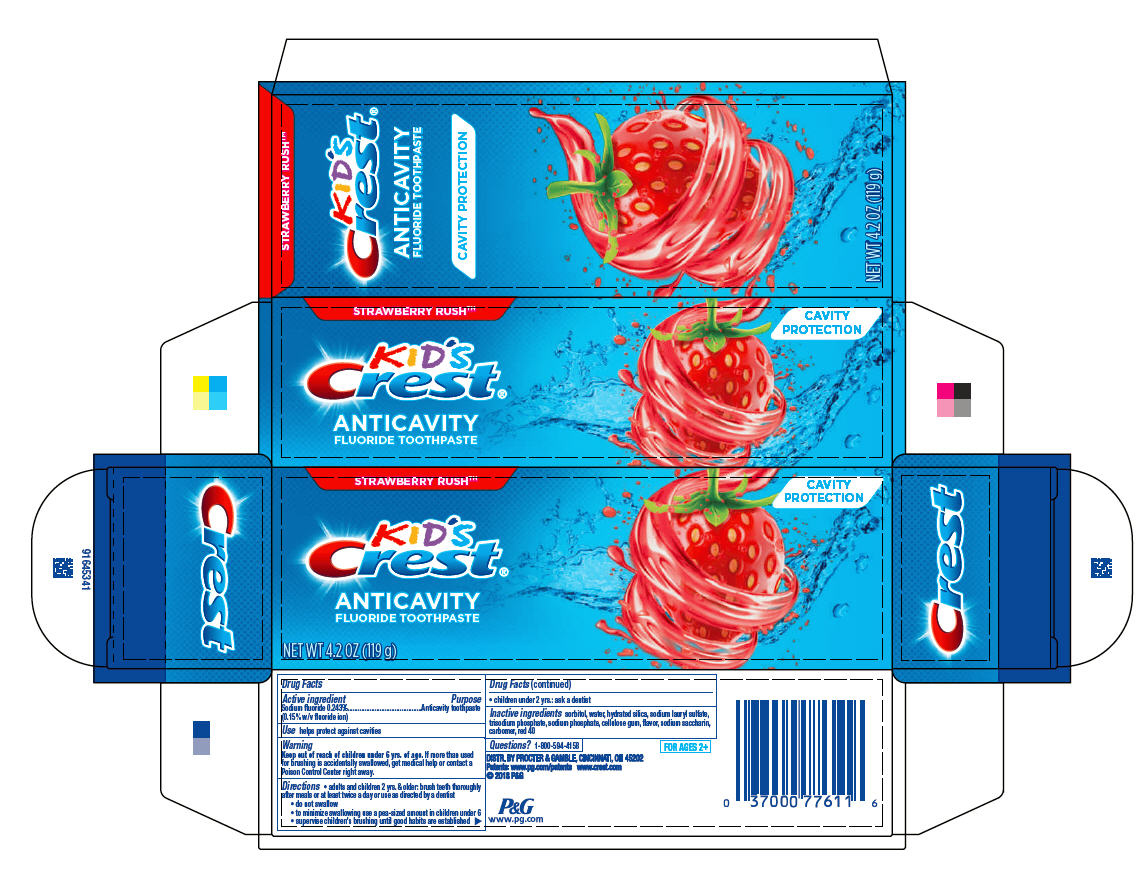 DRUG LABEL: Kids Crest
NDC: 37000-511 | Form: PASTE, DENTIFRICE
Manufacturer: The Procter & Gamble Manufacturing Company
Category: otc | Type: HUMAN OTC DRUG LABEL
Date: 20250806

ACTIVE INGREDIENTS: SODIUM FLUORIDE 1.5 mg/1 g
INACTIVE INGREDIENTS: CARBOXYPOLYMETHYLENE; SACCHARIN SODIUM; SORBITOL; WATER; HYDRATED SILICA; SODIUM LAURYL SULFATE; SODIUM PHOSPHATE; CARBOXYMETHYLCELLULOSE SODIUM; SODIUM PHOSPHATE, TRIBASIC, ANHYDROUS; FD&C RED NO. 40

Kid's
Crest®
Strawberry Rush ™

Drug Facts

Active ingredient

Sodium fluoride 0.243% (0.15% w/v fluoride ion)

Purpose

Anticavity toothpaste

Use

helps protect against cavities

Warnings

Keep out of reach of children under 6 yrs. of age.

WHEN USING

If more than used for brushing is accidentally swallowed, get medical help or contact a Poison Control Center right away.

Directions

- adults and children 2 yrs. & older: brush teeth thoroughly after meals or at least twice a day or use as directed by a dentist
  - do not swallow
  - to minimize swallowing use a pea-sized amount in children under 6
  - supervise children's brushing until good habits are established
- children under 2 yrs.: ask a dentist

Inactive ingredients

sorbitol, water, hydrated silica, sodium lauryl sulfate, trisodium phosphate, sodium phosphate, cellulose gum, flavor, sodium saccharin, carbomer, red 40

Questions?

1-800-594-4158

PRINCIPAL DISPLAY PANEL - 119 g Tube Carton

STRAWBERRY RUSH™

CAVITY
PROTECTION

KID'S
Crest®

ANTICAVITY
FLUORIDE TOOTHPASTE

NET WT 4.2 OZ (119 g)